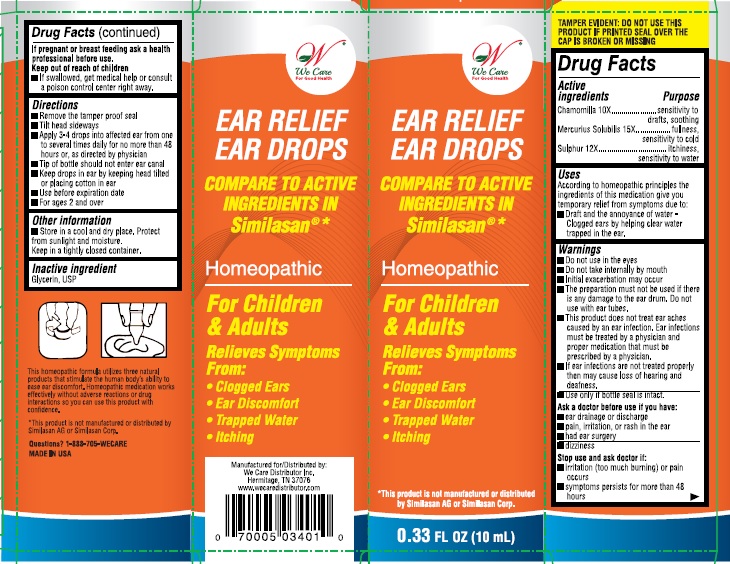 DRUG LABEL: Ear Relief Ear Drops
NDC: 70005-034 | Form: SOLUTION
Manufacturer: We Care Distributor Inc.
Category: homeopathic | Type: HUMAN OTC DRUG LABEL
Date: 20160923

ACTIVE INGREDIENTS: CHAMOMILE 10 [hp_X]/10 mL; MERCURIUS SOLUBILIS 15 [hp_X]/10 mL; SULFUR 12 [hp_X]/10 mL
INACTIVE INGREDIENTS: GLYCERIN

Ear Relief Ear Drops

Active ingredient

Chamomilla 10X

Purpose

sensitivity to drafts, soothing

Active ingredient

Mercurius solubilis 15X

Purpose

fullness, sensitivity to cold

Active ingredient

Sulphur 12X

Purpose

itchiness, sensitivity to water

Uses:

According to homeopathic principles the ingredients of this medication give you temporary relief from symptoms due to:

- drafts and the annoyance of water-clogged ears by helping clear water trapped in the ear.

Warnings:

- Do not use in the eyes.
- Do not take internally by mouth
- Initial exacerbation may occur.
- The preparation must not be used if there is any damage to the ear drum, do not use with ear tubes.
- This product does not treat ear aches caused by an ear infection. Ear infections must be treated by a physician and proper medication that must be prescribed by a physician.
- If ear infections are not treated properly then may cause loss of hearing and deafness.
- Use only if bottle seal in intact.

Ask a doctor before use if you have:

- ear drainage or discharge
- pain, irritation, or rash in the ear
- had ear surgery
- dizzines

Stop use and ask a doctor if:

- irritation (too much burning) or pain occurs
- symptoms persist for more than 48 hours

If pregnant or breast feeding;

ask a health professional before use.

Keep out of reach of children.

If swallowed, get medical help or consult a Poison Control Center right away.

Directions:

- Remove tamper proof seal
- Tilt head sideways
- Apply 3-4 drops into affected ear from one to several times daily for no more than 48 hours, or as directed by a physician
- Tip of the bottle should not enter ear canal
- Keep drops in ear by keeping head tilted or placing cotton in ear.
- Use before expiration date
- For ages 2 and over

Other information:

- Store in a cool and dry place, Protect from sunlight and moisture
- Keep in a tightly closed container

Inactive ingredient:

Glycerin, USP

Questions?

1-888-705-WECARE (Mon-Fri 9am-5pm EST) or www.wecaredistributor.com

PRINCIPAL DISPLAY PANEL

Ear Relief Ear Drops
EAR DROPS
10 ml / 0.33 fl oz